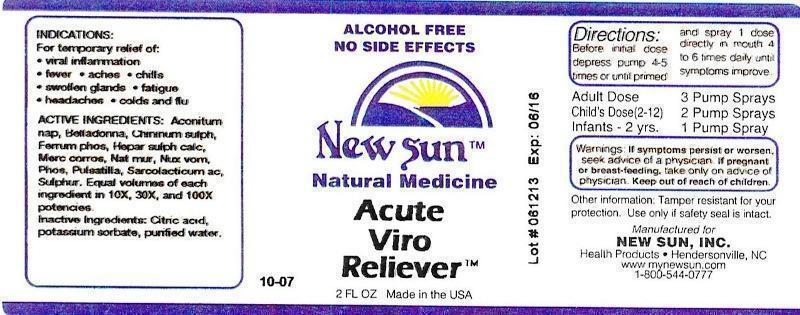 DRUG LABEL: Acute Viro Reliever
NDC: 66579-0019 | Form: LIQUID
Manufacturer: New Sun Inc.
Category: homeopathic | Type: HUMAN OTC DRUG LABEL
Date: 20140905

ACTIVE INGREDIENTS: ACONITUM NAPELLUS 10 [hp_X]/59 mL; ATROPA BELLADONNA 10 [hp_X]/59 mL; QUININE SULFATE 10 [hp_X]/59 mL; FERROSOFERRIC PHOSPHATE 10 [hp_X]/59 mL; CALCIUM SULFIDE 10 [hp_X]/59 mL; MERCURIC CHLORIDE 10 [hp_X]/59 mL; SODIUM CHLORIDE 10 [hp_X]/59 mL; STRYCHNOS NUX-VOMICA SEED 10 [hp_X]/59 mL; PHOSPHORUS 10 [hp_X]/59 mL; PULSATILLA VULGARIS 10 [hp_X]/59 mL; LACTIC ACID, L- 10 [hp_X]/59 mL; SULFUR 10 [hp_X]/59 mL
INACTIVE INGREDIENTS: CITRIC ACID MONOHYDRATE; POTASSIUM SORBATE; WATER

Acute Viro Reliever

DOSAGE AND ADMINISTRATION

Directions: Before initial dose depress pump 4-5 times or until primed and spray 1 dose directly in mouth 4 to 6 times daily until symptoms improve.

Adult Dose: 3 Pump Sprays

Child's Dose (2-12): 2 Pump Sprays

Infants - 2 yrs: 1 Pump Spray

WARNINGS

Warnings: If symptoms persist or worsen, seek advice of a physician. If pregnant or breast-feeding, take only on advice of physician.

Keep out of reach of children.

Other information: Tamper resistant for your protection. Use only if safety seal is intact.

PURPOSE

Indications: For temporary relief of: •viral inflammation •fever •aches •chills •swollen glands •fatigue •headaches •colds and flu

ACTIVE INGREDIENT

Active Ingredients: Aconitum napellus, Belladonna, Chininum sulphuricum, Ferrum phosphoricum, Hepar sulphuris calcareum, Mercurius corrosivus, Natrum muriaticum, Nux vomica, Phosphorus, Pulsatilla, Sarcolacticum acidum, Sulphur. Equal volumes of each ingredient in 10X, 30X, 100X potencies.

Inactive Ingredient: Citric acid, potassium sorbate, purified water.

Indications: For temporary relief of:

- viral inflammation
- fever
- aches
- chills
- swollen glands
- fatigue
- headaches
- colds and flu